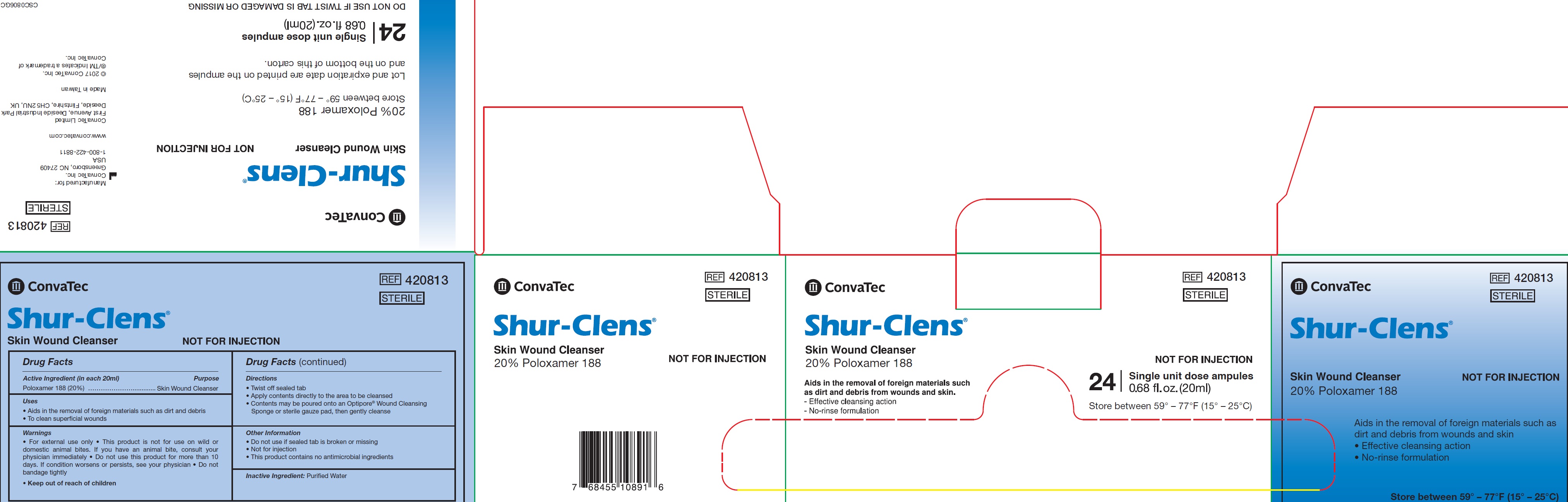 DRUG LABEL: Shur Clens Skin Wound Cleanser 24 Count Single Dose Ampules
NDC: 43553-0000 | Form: LIQUID
Manufacturer: ConvaTec Inc
Category: otc | Type: HUMAN OTC DRUG LABEL
Date: 20210111

ACTIVE INGREDIENTS: POLOXAMER 188 200 mg/1 mL
INACTIVE INGREDIENTS: WATER

Shur-Clens Skin Wound Cleanser 24 Count Single Dose Ampules

Active Ingredient (in each 20ml)

Poloxamer 188 (20%)

Purpose

Skin Wound Cleanser

Uses

• Aids in the removal of foreign materials such as dirt and debris
• To clean superficial wounds

Warnings

• For external use only • This product is not for use on wild or domestic animal bites. If you have an animal bite, consult your physician immediately • Do not use this product for more than 10 days. If condition worsens or persists, see your physician • Do not bandage tightly

Directions

• Twist off sealed tab
• Apply contents directly to the area to be cleansed
• Contents may be poured onto an Optipore® Wound Cleansing Sponge or sterile gauze pad, then gently cleanse

Other Information

• Do not use if sealed tab is broken or missing
• Not for injection
• This product contains no antimicrobial ingredients

Inactive Ingredient:

Purified Water